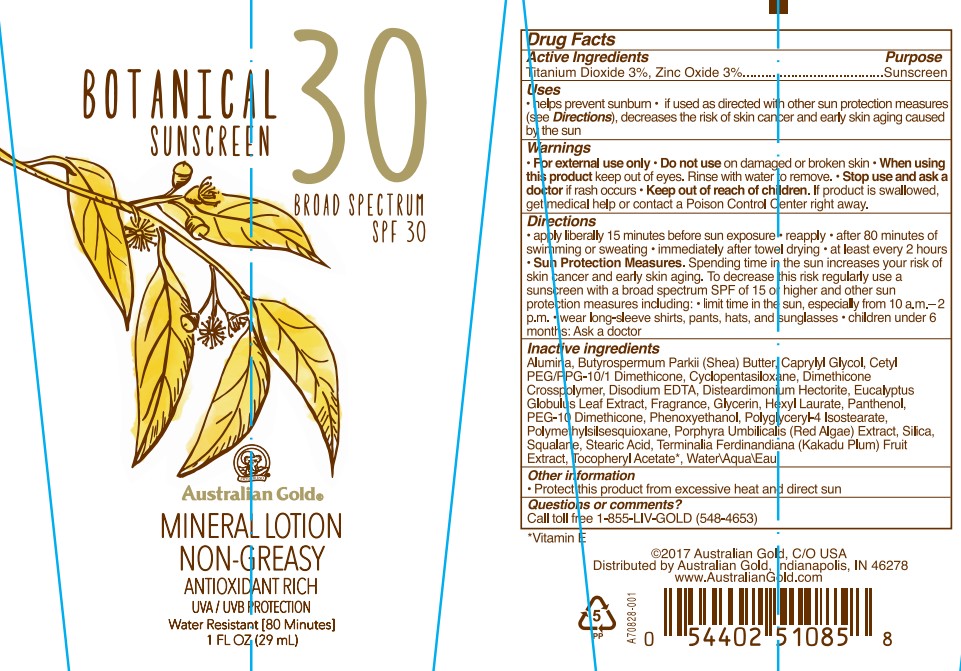 DRUG LABEL: Australian Gold
NDC: 58443-0572 | Form: LOTION
Manufacturer: Prime Enterprises Inc.
Category: otc | Type: HUMAN OTC DRUG LABEL
Date: 20220907

ACTIVE INGREDIENTS: ZINC OXIDE 31.5 mg/1 mL; TITANIUM DIOXIDE 31.5 mg/1 mL
INACTIVE INGREDIENTS: SILICON DIOXIDE; STEARIC ACID; KAKADU PLUM; SQUALANE; POLYMETHYLSILSESQUIOXANE (4.5 MICRONS); PORPHYRA UMBILICALIS; EDETATE DISODIUM; ALUMINUM OXIDE; SHEA BUTTER; CAPRYLYL GLYCOL; CETYL PEG/PPG-10/1 DIMETHICONE (HLB 2); CYCLOMETHICONE 5; DIMETHICONE CROSSPOLYMER (450000 MPA.S AT 12% IN CYCLOPENTASILOXANE); DISTEARDIMONIUM HECTORITE; EUCALYPTUS GLOBULUS LEAF; GLYCERIN; HEXYL LAURATE; PANTHENOL; ALPHA-TOCOPHEROL ACETATE; PEG-10 DIMETHICONE (600 CST); WATER; PHENOXYETHANOL; POLYGLYCERYL-4 ISOSTEARATE

Australian Gold Botanical Mineral Sunscreen Broad Spectrum SPF 30

Active Ingredients

Titanium Dioxide 3%

Zinc Oxide 3%

Purpose

Sunscreen

Uses

- helps prevent sunburn
- if used as directed with other sun protection measures (see Directions), decreases the risk of skin cancer and early skin aging caused by the sun.

Warnings

For external use only

Do not use on damaged or broken skin

When using this product keep out of eyes. Rinse with water to remove.

Stop use and ask a doctor if rash occurs

Keep out of reach of children. If product is swallowed, get medical help or contact a Poison Control Center right away.

Directions

- apply liberally 15 minutes before sun exposure
- reapply:
- after 80 minutes of swimming or sweating
- immediately after towel drying
- at least every 2 hours
- Sun Protection Measures. Spending time in the sun increases your risk of skin cancer and early skin aging. To decrease this risk, regularly use a sunscreen with broad spectrum SPF of 15 or higher and other sun protection measures including:
- limit time in the sun, especially from 10 a.m. – 2 p.m.
- wear long-sleeve shirts, pants, hats, and sunglasses
- children under 6 months: Ask a doctor

INACTIVE INGREDIENT

Alumina, Butyrospermum Parkii (Shea) Butter, Caprylyl Glycol, Cetyl PEG/PPG-10/1 Dimethicone, Cyclopentasiloxane, Dimethicone Crosspolymer, Disodium EDTA, Disteardimonium Hectorite, Eucalyptus Globulus Leaf Extract, Fragrance, Glycerin, Hexyl Laurate, Panthenol, PEG-10 Dimethicone, Phenoxyethanol, Polyglyceryl-4 Isostearate, Polymethylsilsesquioxane, Porphyra Umbilicalis Extract, Silica, Squalane, Stearic Acid, Terminalia Ferdinandiana (Kakadu Plum) Fruit Extract, Tocopheryl Acetate, Water

Other Information

- Protect this product from excessive heat and direct sun

Questions or Comments?

Call toll free 1-855-LIV-GOLD (548-4653)